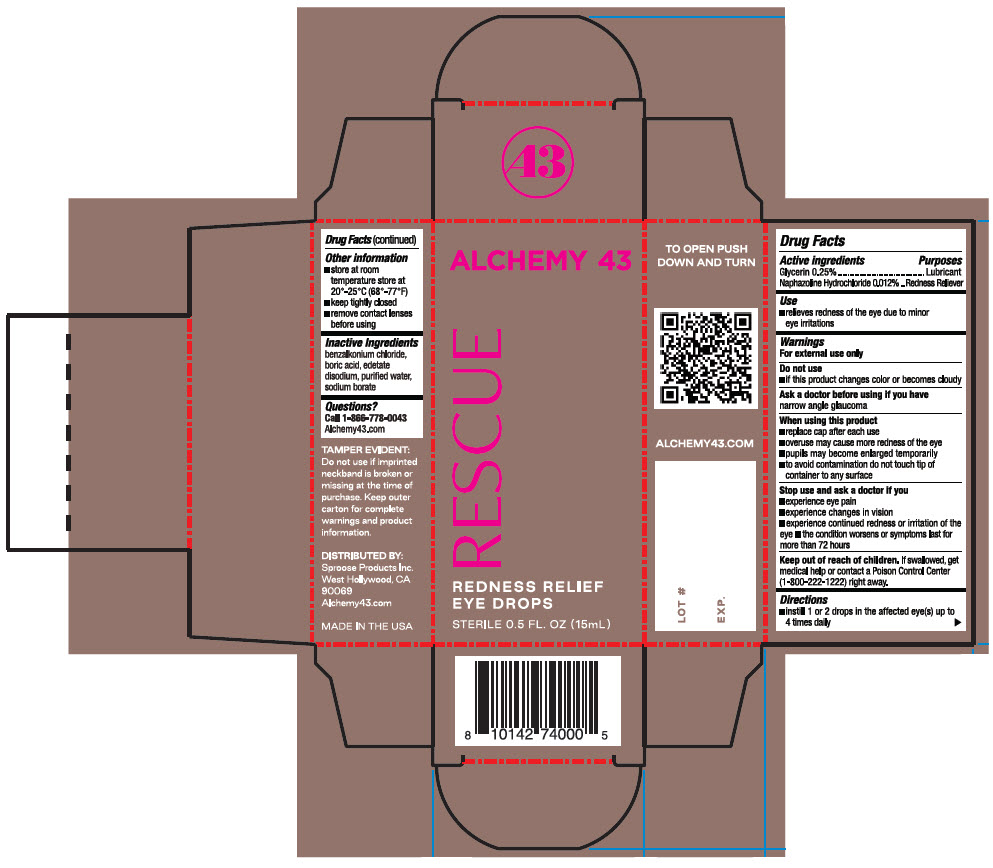 DRUG LABEL: Alchemy 43 Rescue Redness Relief
NDC: 83716-6001 | Form: SOLUTION/ DROPS
Manufacturer: Sproose Products Inc.
Category: otc | Type: HUMAN OTC DRUG LABEL
Date: 20240308

ACTIVE INGREDIENTS: GLYCERIN 0.0025 g/1 mL; NAPHAZOLINE HYDROCHLORIDE 0.00012 g/1 mL
INACTIVE INGREDIENTS: BENZALKONIUM CHLORIDE; BORIC ACID; EDETATE DISODIUM; WATER; SODIUM BORATE

Alchemy 43 Rescue Redness Relief

Drug Facts

ACTIVE INGREDIENT

PURPOSE

Active Ingredients | Purposes
Glycerin 0.25% | Lubricant
Naphazoline hydrochloride 0.012% | Redness Reliever

Use

- relieves redness of the eye due to minor eye irritations

Warnings

For external use only

Do not use

- if this product changes color or becomes cloudy

Ask a doctor before using if you have narrow angle glaucoma

When using this product

- replace cap after each use
- overuse may cause more redness of the eye
- pupils may become enlarged temporarily
- to avoid contamination do not touch tip of container to any surface

Stop use and ask a doctor if you

- experience eye pain
- experience changes in vision
- experience continued redness or irritation of the eye
- the condition worsens or symptoms last for more than 72 hours

Keep out of reach of children. If swallowed, get medical help or contact a Poison Control Center (1-800-222-1222) right away.

Directions

Instill 1 or 2 drops in the affected eye(s) up to 4 times daily

Other information

- Store at room temperature store at 25°-25°C (68°-77°F)
- keep tightly closed
- remove contact lenses before using

Inactive Ingredients

benzalkonium chloride, boric acid, edetate disodium, purified water, sodium borate

Questions?

Call 866-778-0043 Alchemy43.com

Distributed by:
Sproose Products Inc.
West Hollywood, CA 90069

PRINCIPAL DISPLAY PANEL - 15 mL Bottle Carton

ALCHEMY 43

RESCUE

REDNESS RELIEF
EYE DROPS

STERILE 0.5 FL. OZ (15mL)